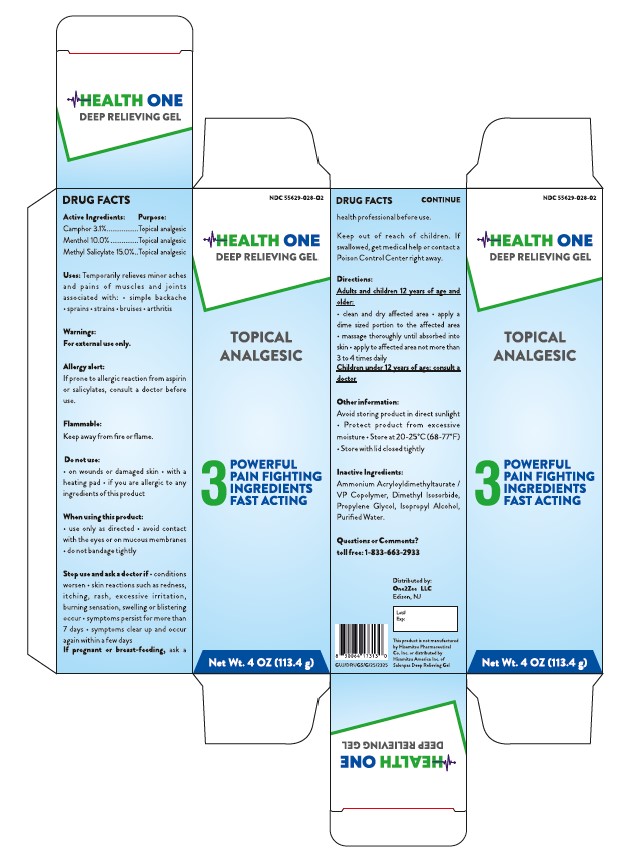 DRUG LABEL: Health One Deep Relieving Gel
NDC: 55629-028 | Form: CREAM
Manufacturer: ONE2ZEE LIMITED LIABILITY COMPANY
Category: otc | Type: HUMAN OTC DRUG LABEL
Date: 20251203

ACTIVE INGREDIENTS: MENTHOL 0.1 g/1 g; CAMPHOR (NATURAL) 0.031 g/1 g; METHYL SALICYLATE .15 g/1 g
INACTIVE INGREDIENTS: AMMONIUM ACRYLOYLDIMETHYLTAURATE; AMMONIUM ACRYLOYLDIMETHYLTAURATE/VP COPOLYMER; DIMETHYL ISOSORBIDE; PROPYLENE GLYCOL; ISOPROPYL ALCOHOL; WATER

Health One Deep Relieving Gel

DRUG FACTS:

Active Ingredients:

Camphor 3.1%

Menthol 10.0%

Methyl Salicylate 15.0%

Purpose

Topical analgesic

Uses

For temporary relief of minor aches and pains of muscles and joints associated with:

- simple backache
- sprains
- strains
- arthritis
- bruises

Warnings

For external use only

Allergy alert:

If prone to allergic reaction from aspirin or salicylates, consult a doctor before use.

Flammable:

Keep away from fire or flame.

Do not use

- on wounds or damaged skin
- with a heating pad
- if you are allergic to any ingredients of this product

When using this product

- use only as directed
- avoid contact with the eyes, mucous membranes or rashes
- do not bandage tightly

Stop use and ask a doctor if

- conditions worsen
- skin reactions such are redness, itching, rash, excessive irritation, burning sensation, swelling or blistering occur
- symptoms persist for more than 7 days
- symptoms clear up and occur again within a few days

If pregnant or breast-feeding.

ask a health professional before use.

Keep out of reach of children.

If swallowed, get medical help or contact a Poison Control Center right away.

Directions

Adults and children 12 years of age and over:

- clean and dry affected area
- apply a dime sized portion to the affected area
- massage thoroughly until absorbed into skin
- apply to affected area not more than 3 to 4 times daily

Children under 12 years of age: consult a doctor

Other information

- Avoid storing product in direct sunlight
- Protect product from excessive moisture
- Store at 20-25C (68-77F)
- Store with lid closed tightly

Inactive ingredients

Ammonium Acryloyldimethyltaurate, VP Copolymer, Dimethyl Isosorbide, Propylene Glycol, Isopropyl Alcohol, Purified Water

Questions or comments?

1-833-663-2933